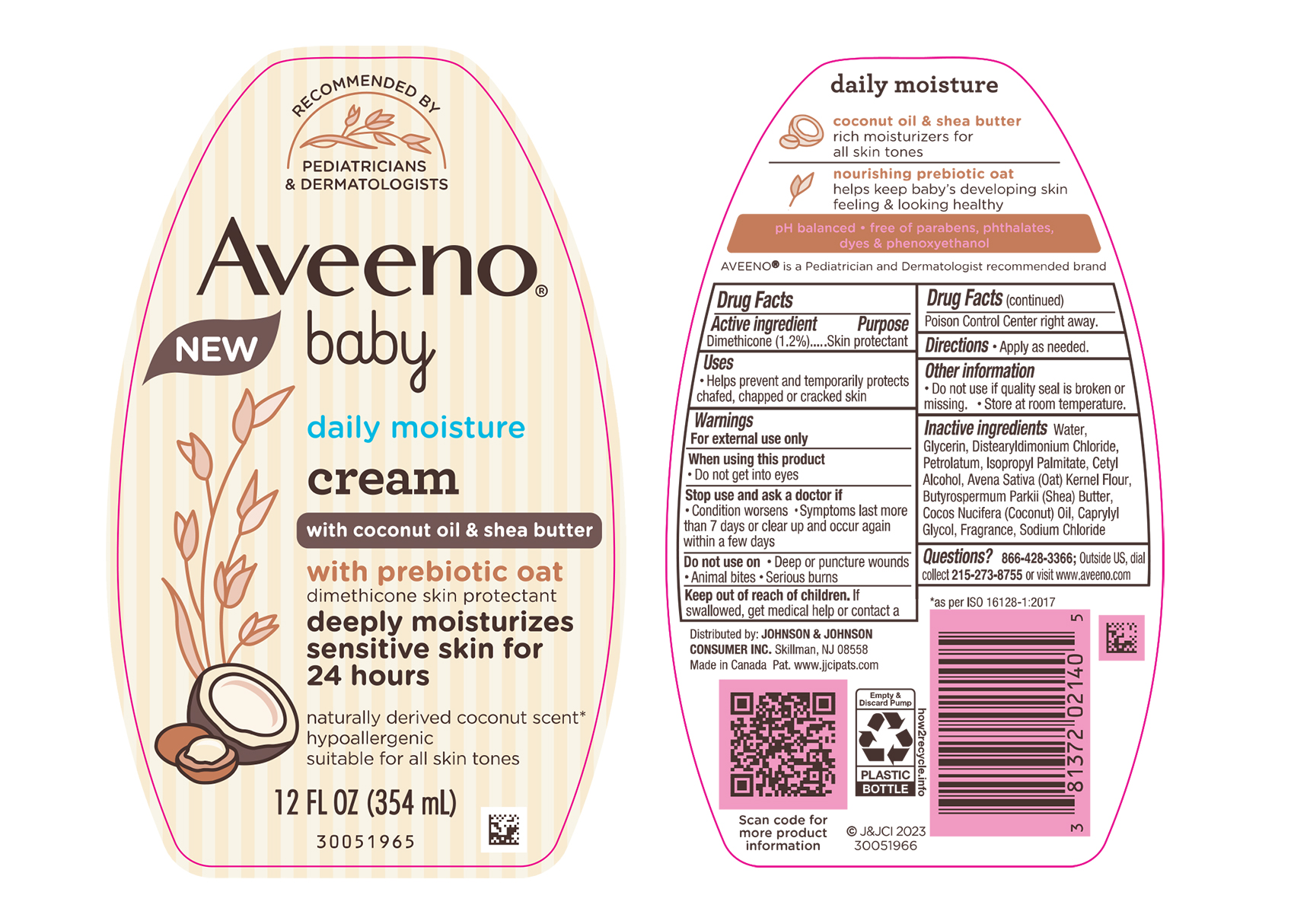 DRUG LABEL: Aveeno Baby Daily Moisture with Coconut Oil and Shea Butter
NDC: 69968-0762 | Form: CREAM
Manufacturer: Kenvue Brands LLC
Category: otc | Type: HUMAN OTC DRUG LABEL
Date: 20241105

ACTIVE INGREDIENTS: DIMETHICONE 12 mg/1 mL
INACTIVE INGREDIENTS: GLYCERIN; DISTEARYLDIMONIUM CHLORIDE; PETROLATUM; SHEA BUTTER; COCONUT OIL; WATER; CAPRYLYL GLYCOL; SODIUM CHLORIDE; ISOPROPYL PALMITATE; CETYL ALCOHOL; OATMEAL

Aveeno Baby Daily Moisture Cream with Coconut Oil & Shea Butter

Drug Facts

Active ingredient

Dimethicone (1.2%)

Purpose

Skin protectant

Uses

- Helps prevent and temporarily protects chafed, chapped or cracked skin

Warnings

For external use only

When using this product

- Do not get into eyes

Stop use and ask a doctor if

- Condition worsens
- Symptoms last more than 7 days or clear up and occur again within a few days

Do not use on

- Deep or puncture wounds
- Animal bites
- Serious burns

Keep out of reach of children. If swallowed, get medical help or contact a Poison Control Center right away.

Directions

- Apply as needed.

Other information

- Do not use if quality seal is broken or missing.
- Store at room temperature.

Inactive ingredients

Water, Glycerin, Distearyldimonium Chloride, Petrolatum, Isopropyl Palmitate, Cetyl Alcohol, Avena Sativa (Oat) Kernel Flour, Butyrospermum Parkii (Shea) Butter, Cocos Nucifera (Coconut) Oil, Caprylyl Glycol, Fragrance, Sodium Chloride

Questions?

866-428-3366; Outside US, dial collect 215-273-8755 or visit www.aveeno.com

Distributed by:
JOHNSON & JOHNSON
CONSUMER INC.
Skillman, NJ 08558

PRINCIPAL DISPLAY PANEL - 354 mL Bottle Label

RECOMMENDED BY

PEDIATRICIANS

& DERMATOLOGISTS

Aveeno®

NEW

baby

daily moisture

cream

with coconut oil & shea butter

with prebiotic oat

dimethicone skin protectant

deeply moisturizes

sensitive skin for

24 hours

naturally derived coconut scent*

hypoallergenic

suitable for all skin tones

12 FL OZ (354 mL)